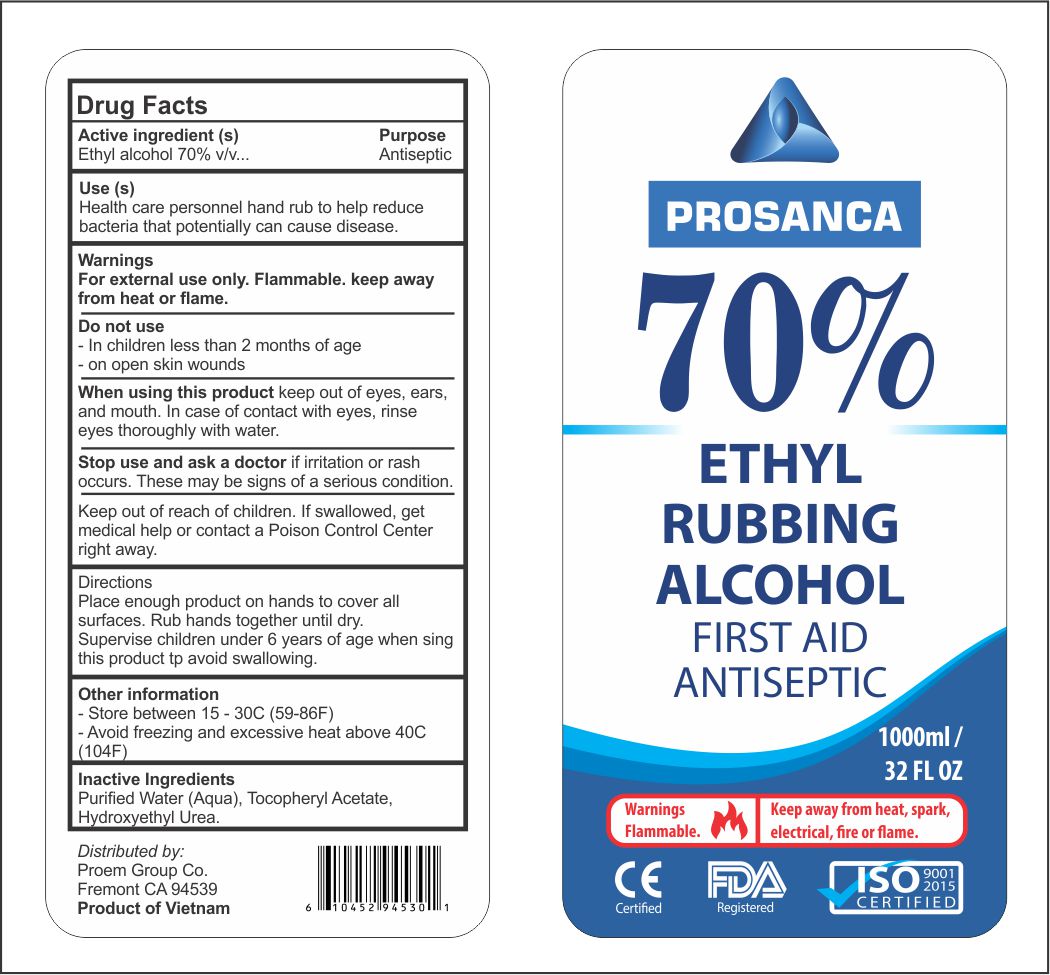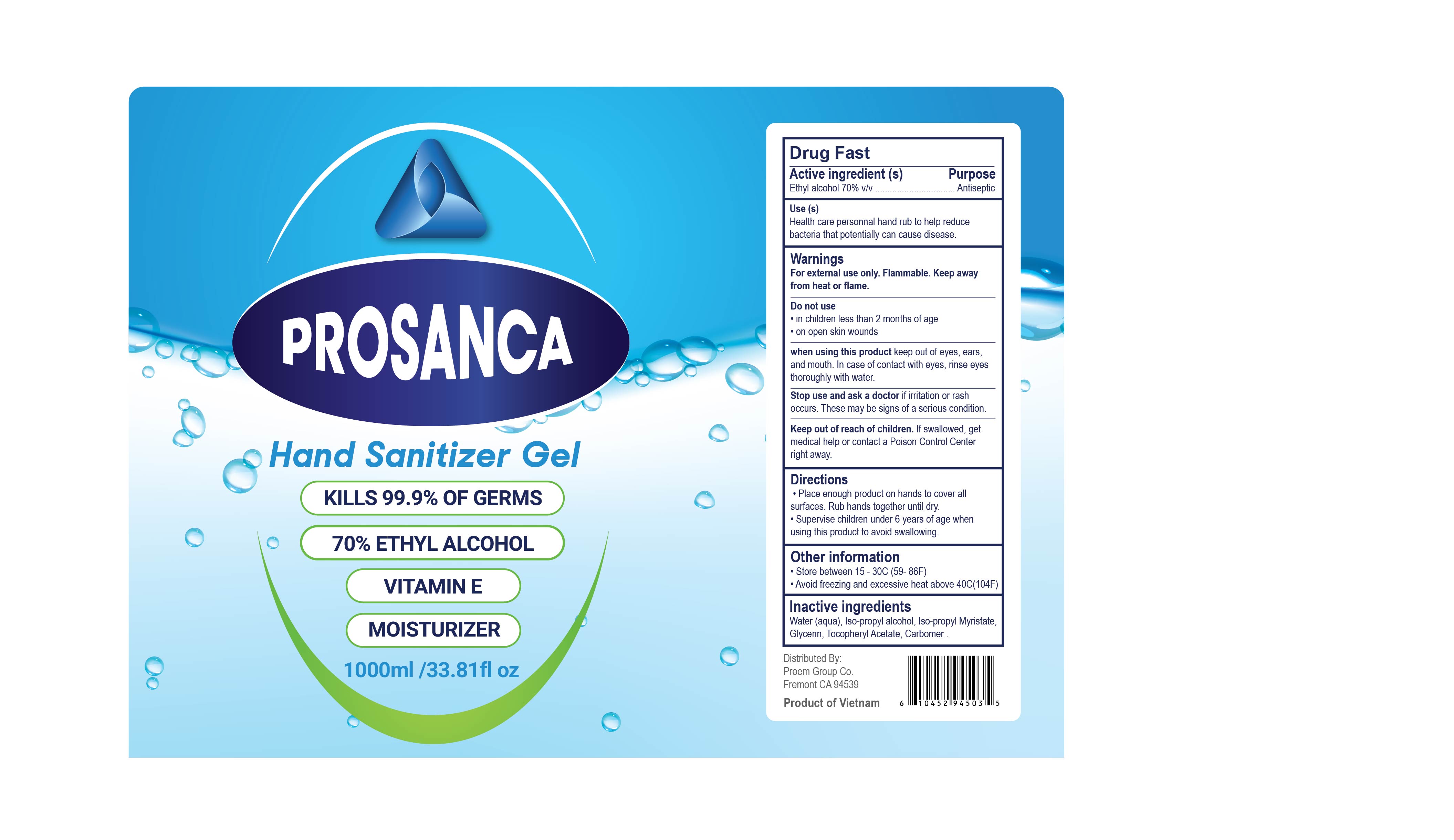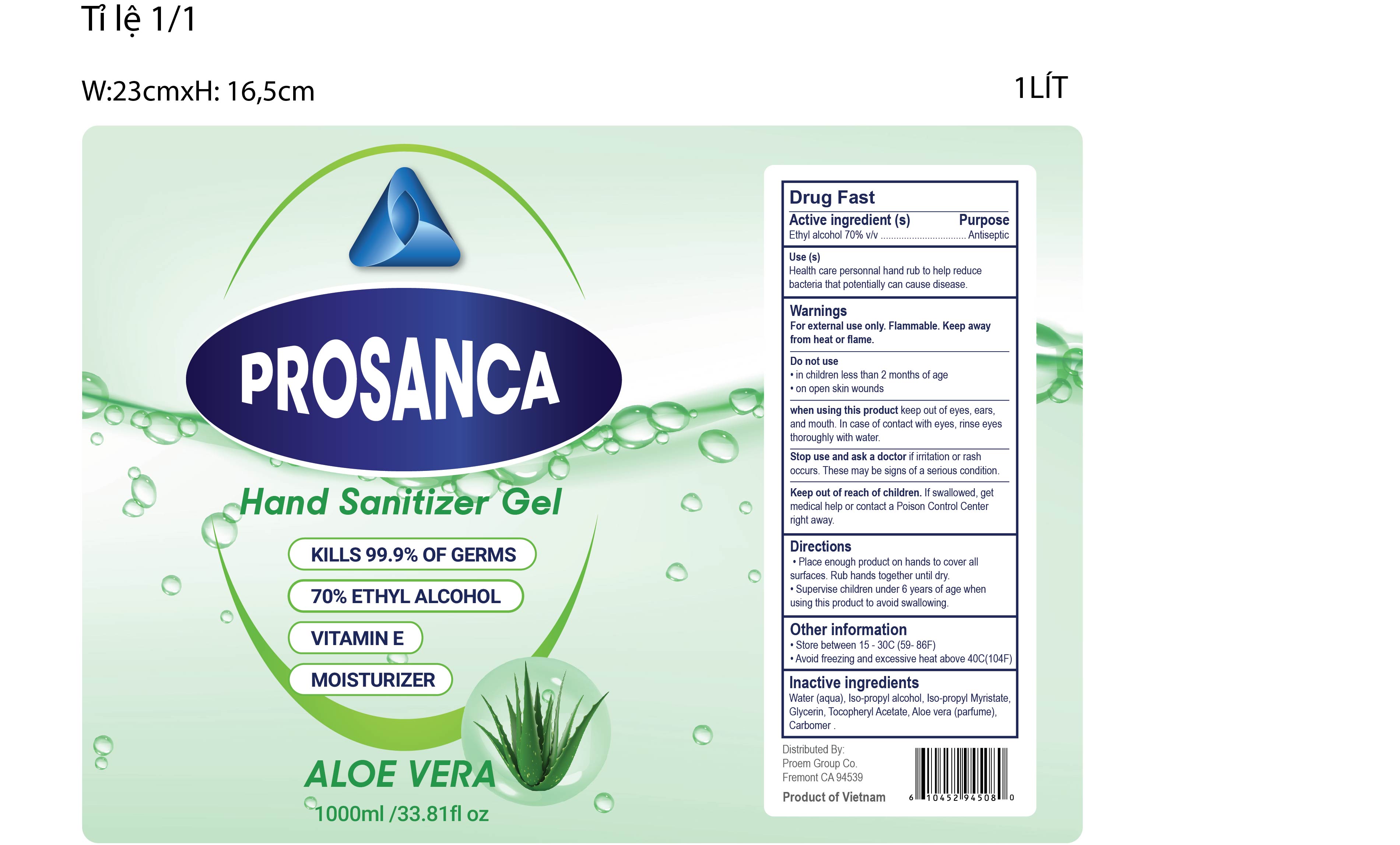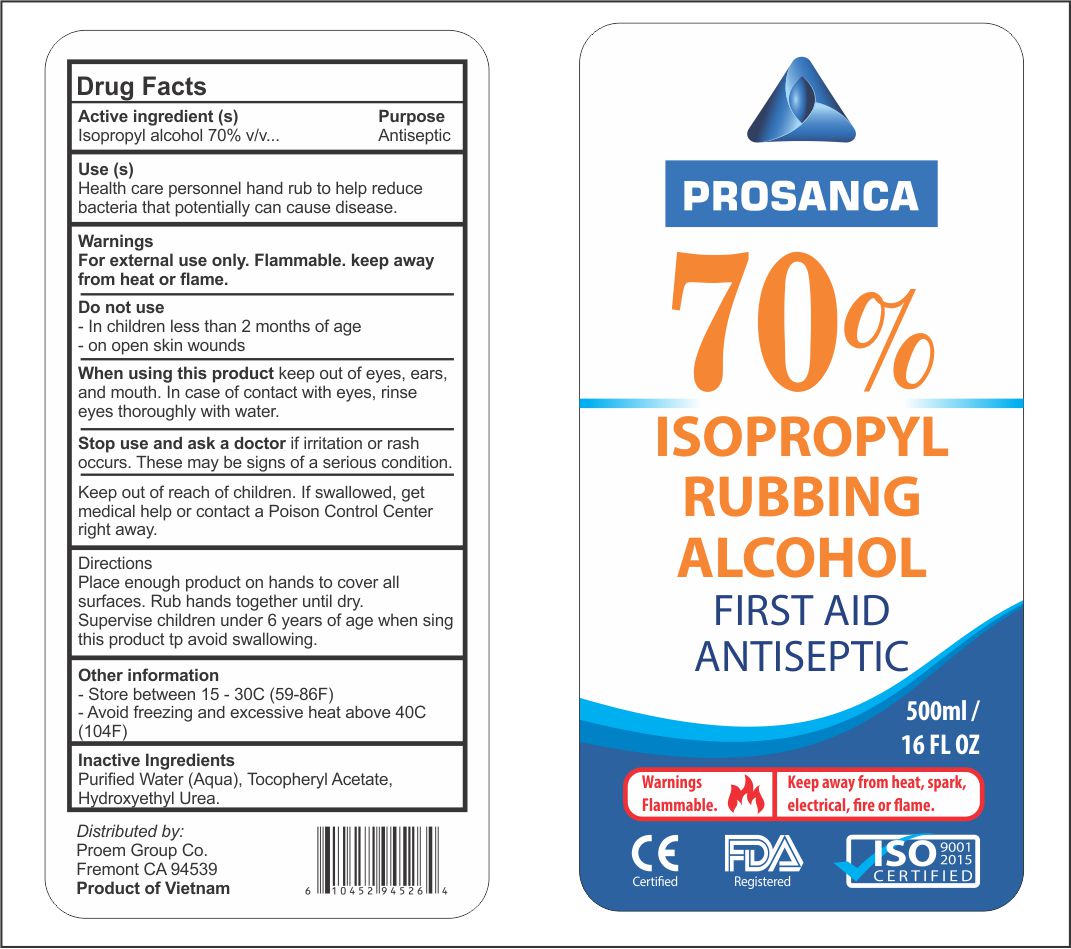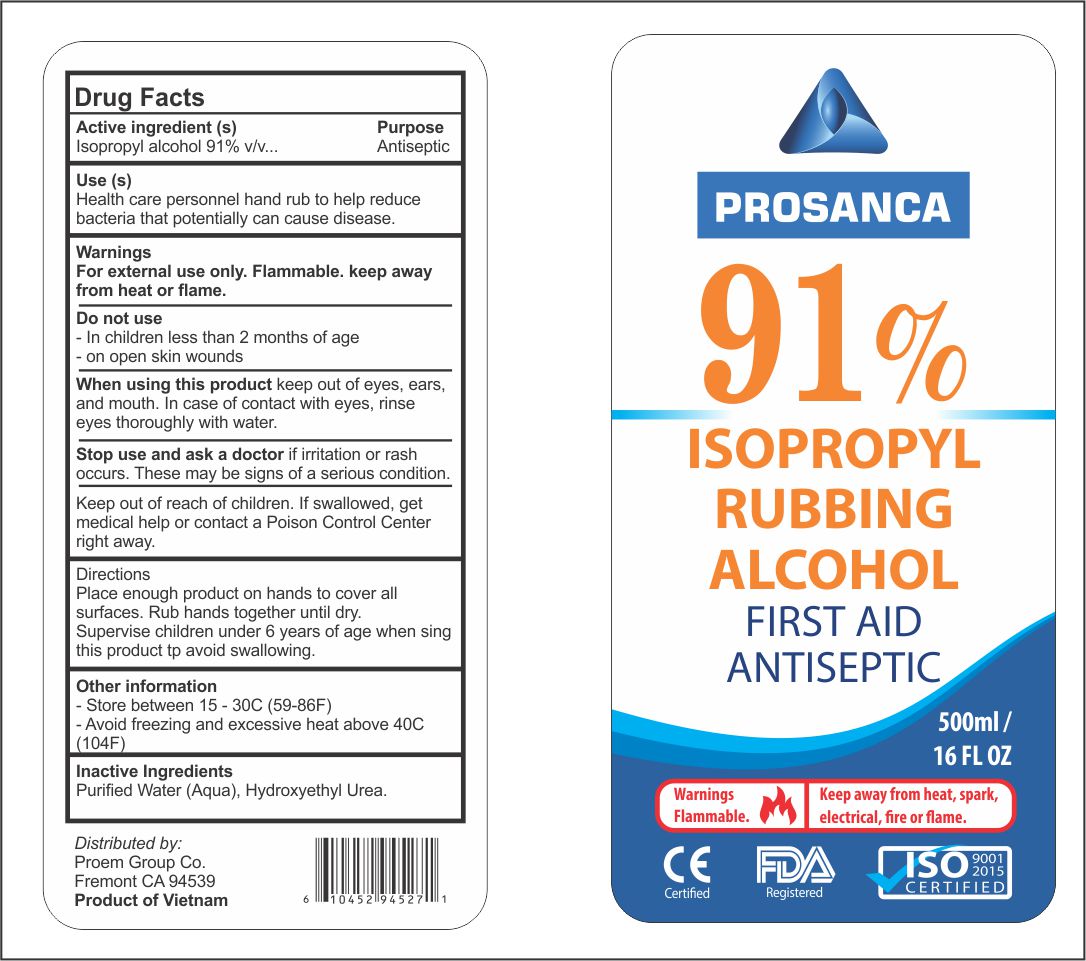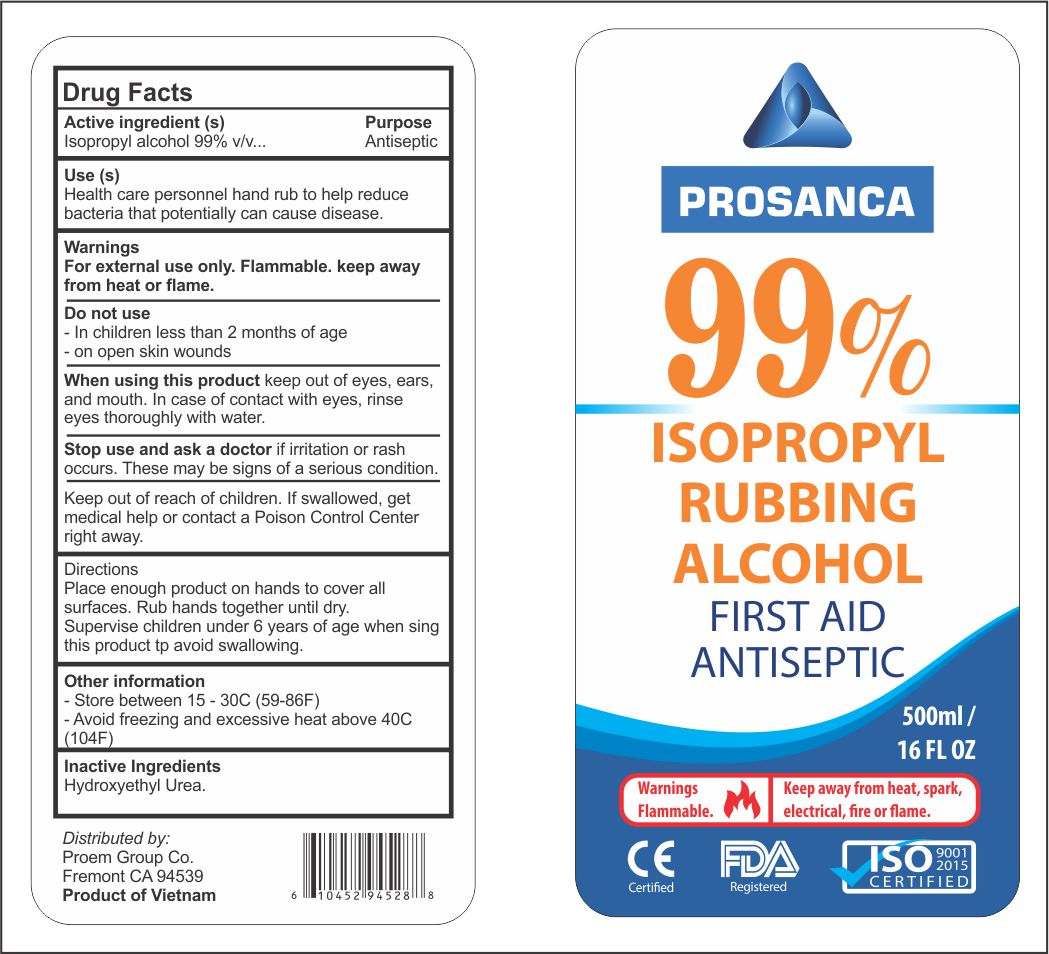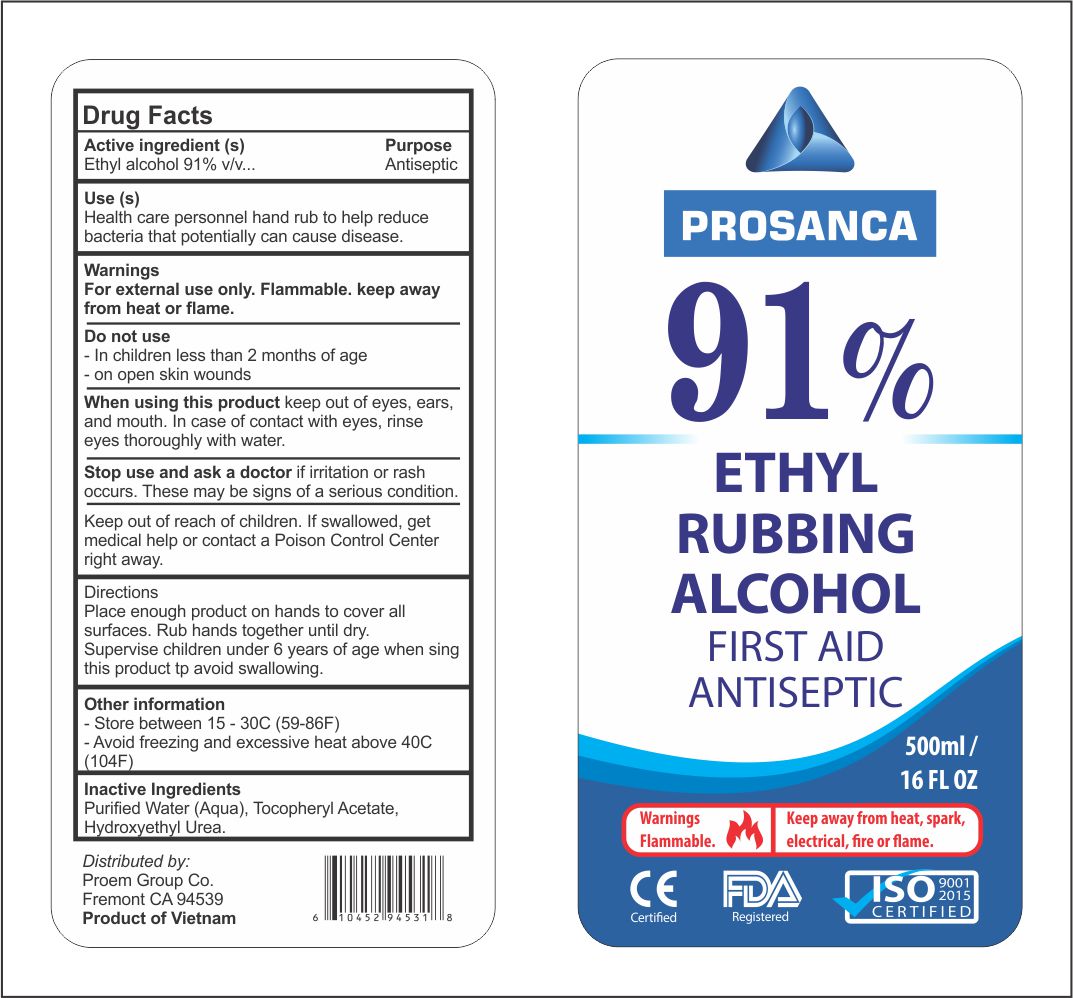 DRUG LABEL: Prosanca
NDC: 77838-336 | Form: GEL
Manufacturer: proem group
Category: otc | Type: HUMAN OTC DRUG LABEL
Date: 20211221

ACTIVE INGREDIENTS: ALCOHOL 70 mL/100 mL
INACTIVE INGREDIENTS: .ALPHA.-TOCOPHEROL ACETATE 0.1 mL/100 mL; GLYCERIN 0.145 mL/100 mL; WATER

Hand Sanitizer and Rubbing Alcohol

ACTIVE INGREDIENT

70% Ethanal, 91% Ethanol, 70% Isopropyl, 91% Isopropyl, 99% Isopropyl.

INACTIVE INGREDIENT

Water, Tocophery Acetate, Hydroxythel Urea

WARNINGS

For external use only, Flammable, Keep away from heat or flam.

Do not use: in children less 2 months of age on open skin wounds

When use this product: this product keep out of eyes,ears and mouth. In case of contact with eyes, rinse eyes thoroughly with water.

Stop use and ask a doctor if irritation or rash occurs, these may be signs of s serious condition

Keep out of reach of children. If swallow get medical or contact of poison Control Center right away

INDICATIONS AND USAGE

Hand Sanitizer to help reduce bateria that potentially can cause disease for use when soap are not available.

Rubbing Alocohol keep out of eyes, ears and mouth. Incase of contact with eyes rinse thorough with water.

KEEP OUT OF REACH OF CHILDREN

If swallow, get medical help or contact o poison control Center right away.

DOSAGE AND ADMINISTRATION

70% Ethanol alcohol, 91% Ethanol Alcohol, 70% Isopropyl, 91% Isopropyl, 99% Isopropyl

PURPOSE

Use Hand Sanitizer to help reduce bacteria that potentially can cause disease. For use when soap are not avalble.